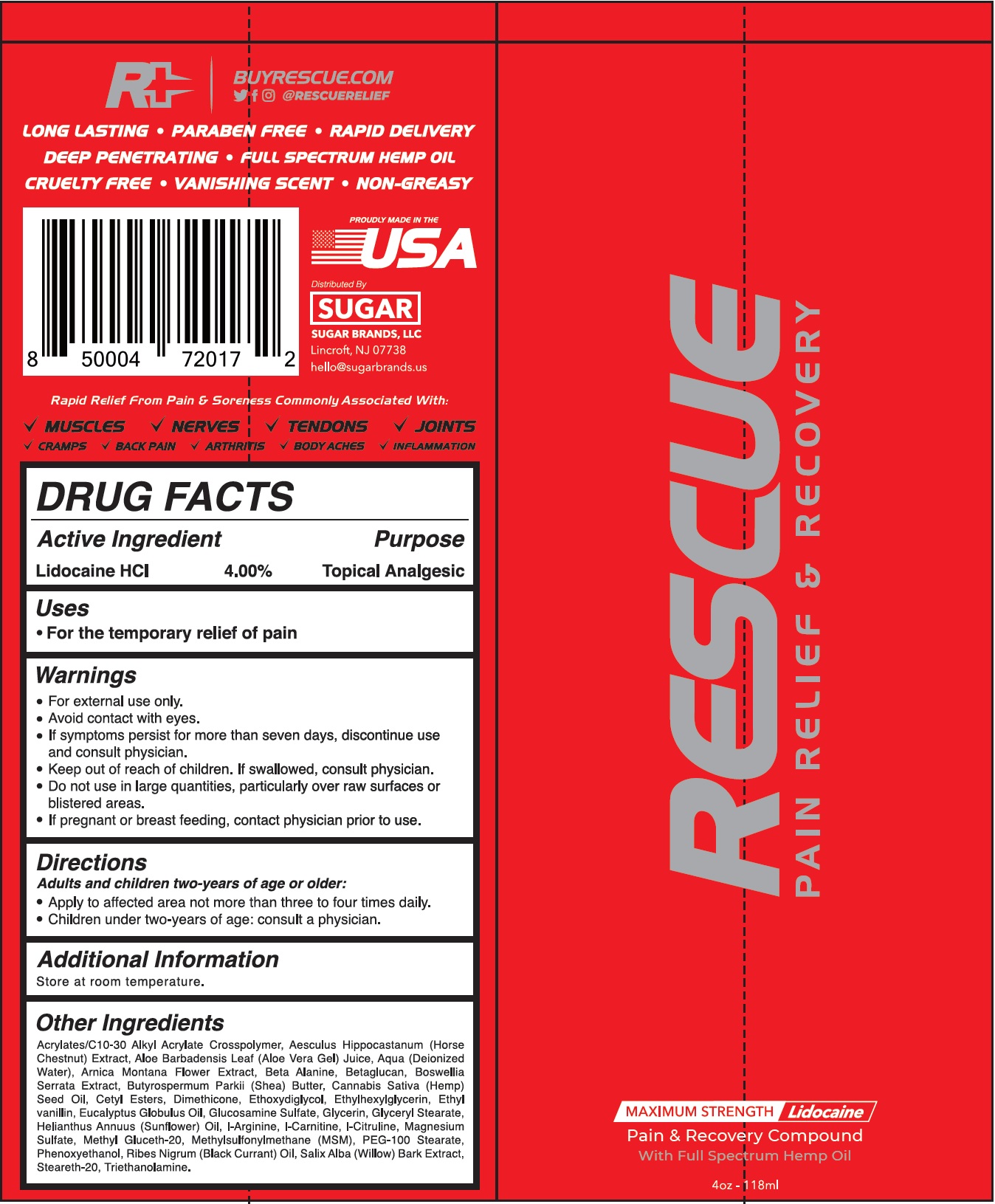 DRUG LABEL: SUGAR BRANDS Rescue Pain Relief and Recovery
NDC: 73313-075 | Form: CREAM
Manufacturer: Sugar Brands, LLC
Category: otc | Type: HUMAN OTC DRUG LABEL
Date: 20231111

ACTIVE INGREDIENTS: LIDOCAINE HYDROCHLORIDE 40 mg/1 mL
INACTIVE INGREDIENTS: CARBOMER INTERPOLYMER TYPE A (ALLYL SUCROSE CROSSLINKED); HORSE CHESTNUT; ALOE VERA LEAF; WATER; ARNICA MONTANA FLOWER; .BETA.-ALANINE; INDIAN FRANKINCENSE; SHEA BUTTER; CANNABIS SATIVA SEED OIL; CETYL ESTERS WAX; DIMETHICONE; DIETHYLENE GLYCOL MONOETHYL ETHER; ETHYLHEXYLGLYCERIN; ETHYL VANILLIN; EUCALYPTUS OIL; GLUCOSAMINE SULFATE; GLYCERIN; GLYCERYL MONOSTEARATE; HELIANTHUS ANNUUS FLOWERING TOP; ARGININE; LEVOCARNITINE; CITRULLINE; MAGNESIUM SULFATE, UNSPECIFIED FORM; METHYL GLUCETH-20; DIMETHYL SULFONE; PEG-100 STEARATE; PHENOXYETHANOL; BLACK CURRANT; SALIX ALBA BARK; STEARETH-20; TROLAMINE

SUGAR BRANDS: Rescue Pain Relief & Recovery Cream

Active Ingredient

Lidocaine HCl 4.00%

Purpose

Topical Analgesic

Uses

- For the temporary relief of pain

Warnings

- For external use only.
- Avoid contact with eyes.
- If symptoms persist for more than seven days, discontinue use and consult physician.

Keep out of reach of children.

If swallowed, consult physician.

Do not use

in large quantities, particularly over raw surfaces or blistered areas.

If pregnant or breast feeding,

contact physician prior to use.

Directions

Adults and children two-years of age or older:

- Apply to affected area not more than three to four times daily.
- Children under two-years of age: consult a physician.

Additional Information

Store at room temperature.

Other Ingredients

Acrylates/C10-30 Alkyl Acrylate Crosspolymer, Aesculus Hippocastanum (Horse Chestnut) Extract, Aloe Barbadensis Leaf (Aloe Vera Gel) Juice, Aqua (Deionized Water), Arnica Montana Flower Extract, Beta Alanine, Betaglucan, Boswellia Serrata Extract, Butyrospermum Parkii (Shea) Butter, Cannabis Sativa (Hemp) Seed Oil, Cetyl Esters, Dimethicone, Ethoxydiglycol, Ethylhexylglycerin, Ethyl Vanillin, Eucalyptus Globulus Oil, Glucosamine Sulfate, Glycerin, Glyceryl Stearate, Helianthus Annuus (Sunflower) Oil, l-Arginine, l-Carnitine, l-Citruline, Magnesium Sulfate, Methyl Gluceth-20, Methylsulfonylmethane (MSM), PEG-100 Stearate, Phenoxyethanol, Ribes Nigrum (Black Currant) Oil, Salix Alba (Willow) Bark Extract, Steareth-20, Triethanolamine.